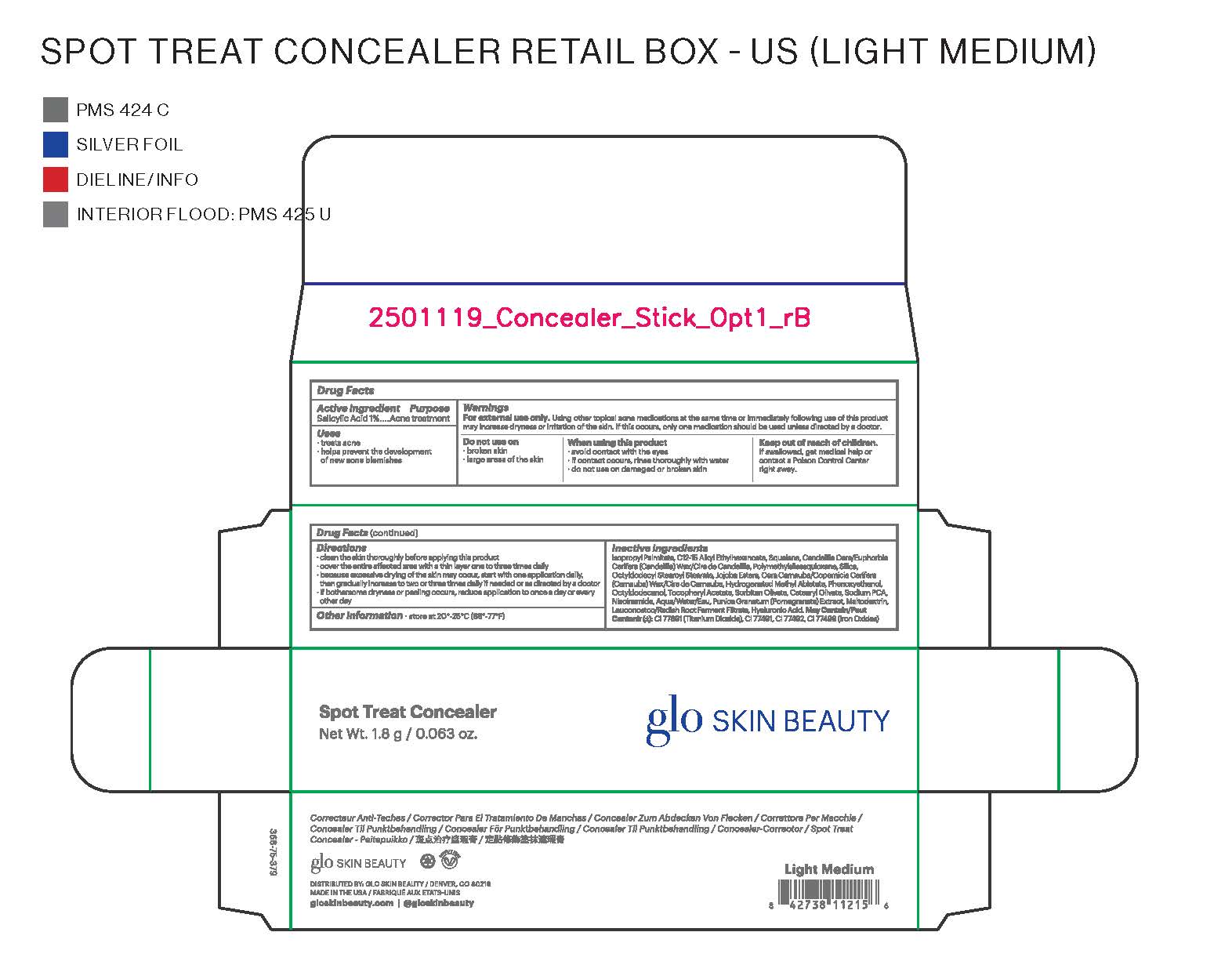 DRUG LABEL: glo SKIN BEAUTY Spot Treat Concealer
NDC: 60541-2100 | Form: LIQUID
Manufacturer: Hayden Caleel LLC
Category: otc | Type: HUMAN OTC DRUG LABEL
Date: 20250922

ACTIVE INGREDIENTS: SALICYLIC ACID 1 g/100 g
INACTIVE INGREDIENTS: LEUCONOSTOC/RADISH ROOT FERMENT FILTRATE; HYALURONIC ACID; ISOPROPYL PALMITATE; C12-15 ALKYL ETHYLHEXANOATE; SQUALANE; EUPHORBIA CERIFERA (CANDELILLA) WAX; POLYMETHYLSILSESQUIOXANE (11 MICRONS); SILICON; OCTYLDODECYL STEAROYL STEARATE; COPERNICIA CERIFERA (CARNAUBA) WAX; HYDROGENATED METHYL ABIETATE; PHENOXYETHANOL; OCTYLDODECANOL; .ALPHA.-TOCOPHEROL ACETATE, DL-; SORBITAN OLIVATE; SODIUM PCA; MALTODEXTRIN; TITANIUM DIOXIDE; WATER; PUNICA GRANATUM WHOLE; CETEARYL OLIVATE; NIACINAMIDE; BROWN IRON OXIDE

glo SKIN BEAUTY Spot Treat Concealer

Active Ingredients

Salicylic Acid 1%

Purpose

Acne Treatment

Uses

- Treats Acne
- Helps prevent the development of new acne blemishes

Warnings

Using other topical acne medications at the same tiem or immediatly following use of this prouct may increase dryness or irritation of the skin. If this occurs, only one medication shoul be used unless directed by a doctor.

For external use only
When using this product
• avoid contact with the eyes
• if contact occurs, rinse thoroughly with water
• do not use on damaged or broken skin

Keep out of reach of children. If swallowed, get medical help
or contact a Poison Control Center right away.

Directions

- Clean the skin thoroughly before applying this product
- Cover the entire affected area with a thin layer one to three times daily
- Because excessive drying of the skin may occur, start with one application daily, then gradually increase to two or three times daily if needed or as directed by a doctor
- If bothersome dryness or peeling occurs, reduce use to once a day or every other ay

Inactive Ingredients

Isopropyl Palmitate, C12-15 Alkyl Ethylhexanoate, Squalane, Candelilla Cera/Euphorbia Cerifera (Candelilla) Wax/Cire de Candelilla, Polymethylsilsesquioxane, Silica, Octyldodecyl Stearoyl Stearate, Jojoba Esters, Cera Carnauba/Copernicia Cerifera (Carnauba) Wax/Cire de Carnauba, Hydrogenated Methyl Abietate, Phenoxyethanol, Salicylic Acid, Octyldodecanol, Tocopheryl Acetate, Sorbitan Olivate, Cetearyl Olivate, Sodium PCA, Niacinamide, Aqua/Water/Eau, Punica Granatum (Pomegranate) Extract, Maltodextrin, Leuconostoc/Radish Root Ferment Filtrate, Hyaluronic Acid. May Contain/Peut Contenir (±): CI 77891 (Titanium Dioxide), CI 77491, CI 77492, CI 77499 (Iron Oxides).